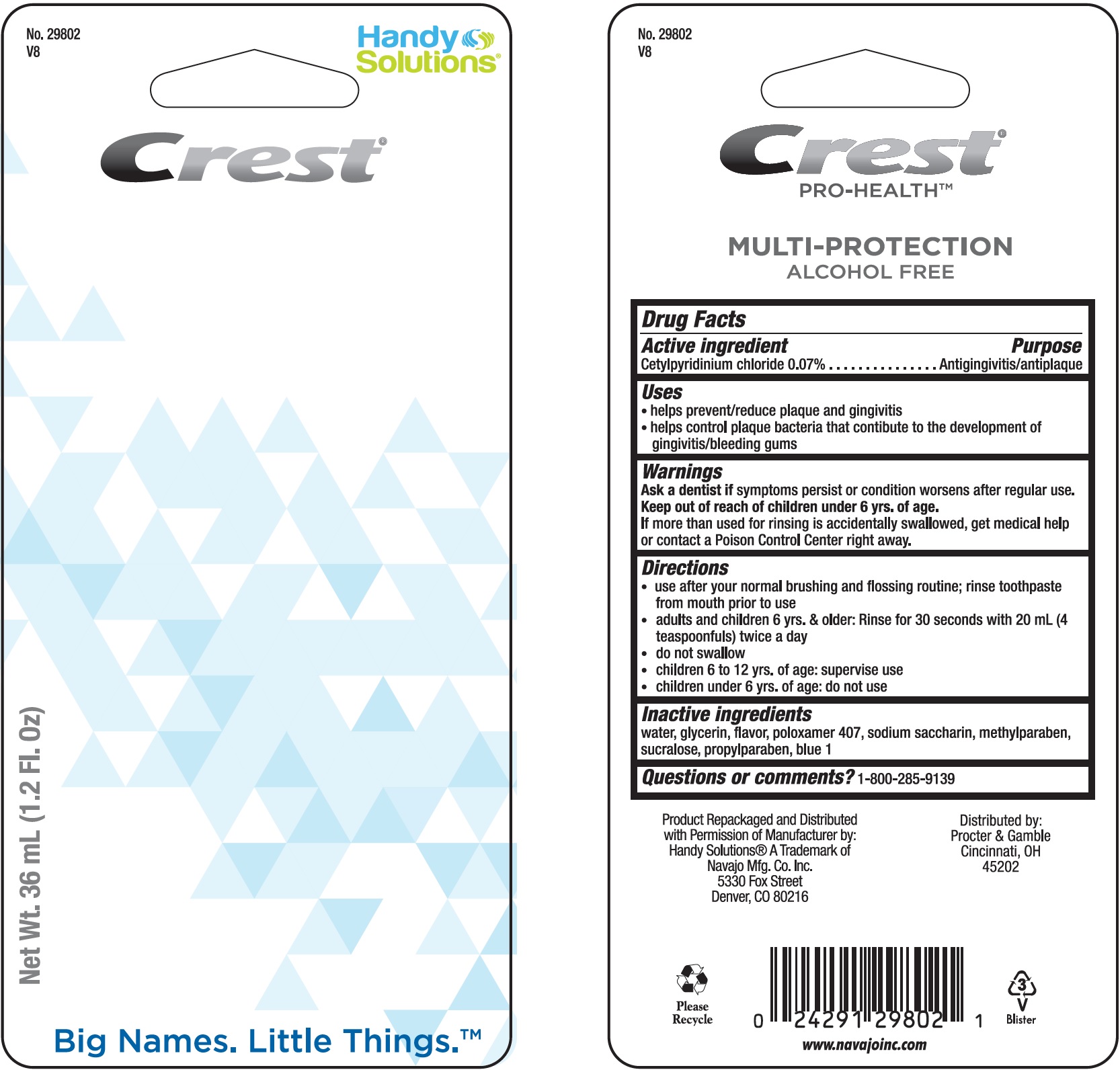 DRUG LABEL: Crest Pro Health
NDC: 67751-186 | Form: RINSE
Manufacturer: Navajo Manufacturing Company Inc.
Category: otc | Type: HUMAN OTC DRUG LABEL
Date: 20241002

ACTIVE INGREDIENTS: CETYLPYRIDINIUM CHLORIDE 0.014 g/20 mL
INACTIVE INGREDIENTS: WATER; GLYCERIN; METHYL SALICYLATE; POLOXAMER 407; SACCHARIN SODIUM; METHYLPARABEN; SUCRALOSE; PROPYLPARABEN; FD&C BLUE NO. 1

Crest Pro Health

Active ingredient

Cetylpyridinium chloride 0.07%

Purpose

Antigingivitis/antiplaque

Uses

- helps prevent/reduce plaque and gingivitis
- helps control plaque bacteria that contibute to the development of gingivitis/bleeding gums

Warnings

Ask a dentist if

symptoms persist or condition worsens after regular use.

Keep out of reach of children.

under 6 yrs. of age. If more than used for rinsing is accidentally swallowed, get medical help or contact a Poison Control Center right away.

Directions

- use after your normal brushing and flossing routine; toothpaste from mouth prior to use
- adults and children 6 yrs. & older: Rinse for 30 seconds with 20 ml (4 teaspoonfuls) twice a day
- do not swallow
- children 6 to 12 yrs. of age: supervise use
- children under 6 yrs. of age: do not use

Inactive ingredients

water, glycerin, flavor, poloxamer 407, sodium saccharin, methylparaben, sucralose, propylparaben, blue 1

Questions or comments?

1-800-285-9139